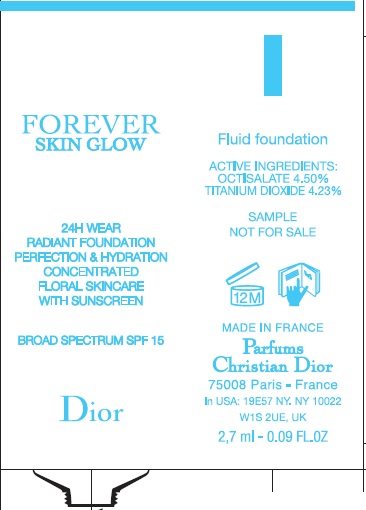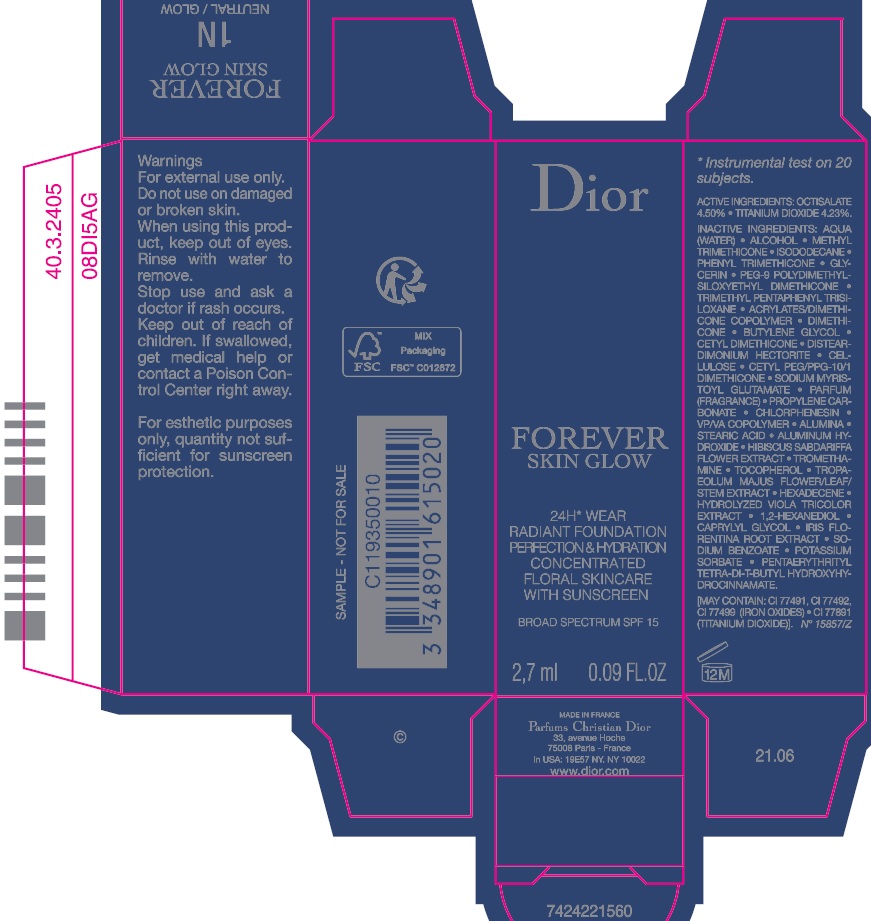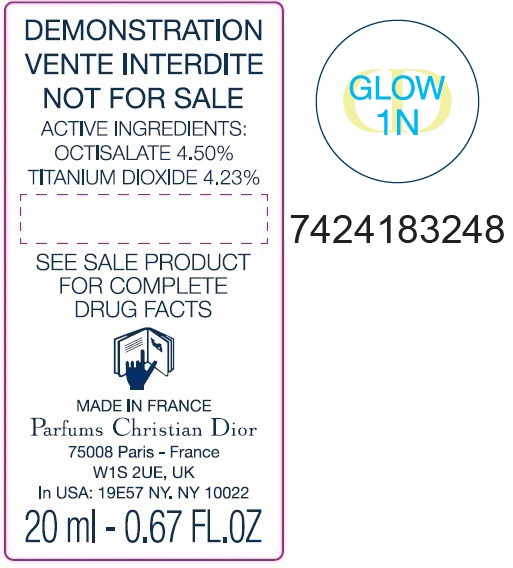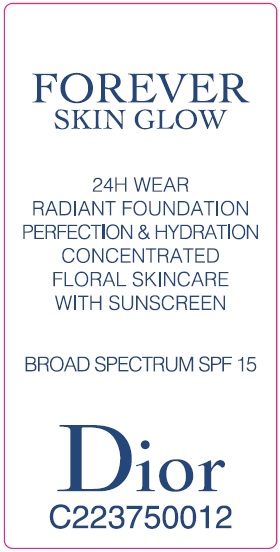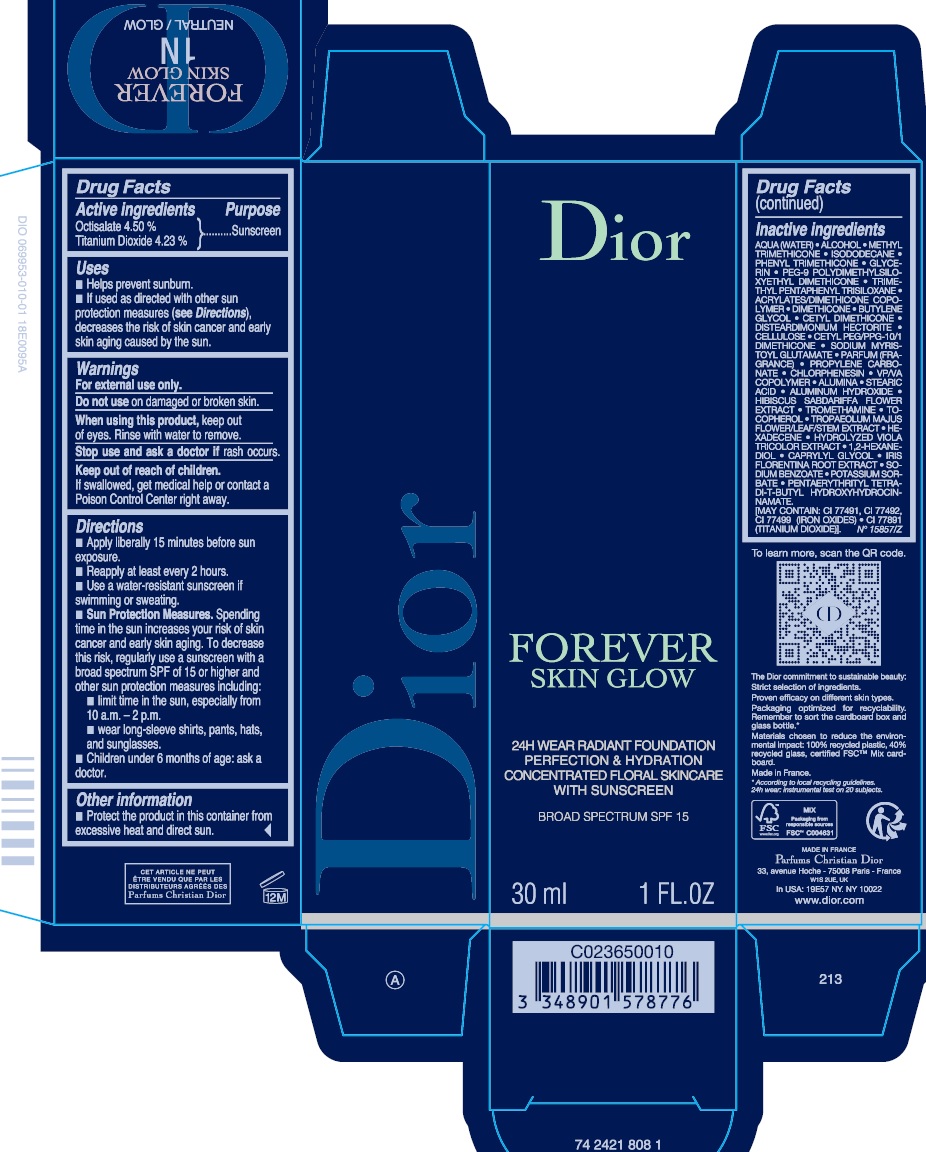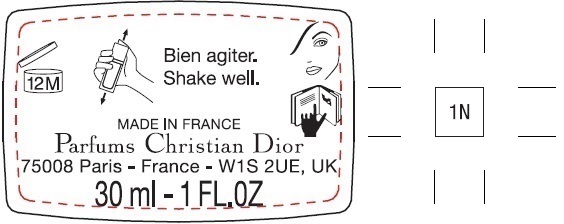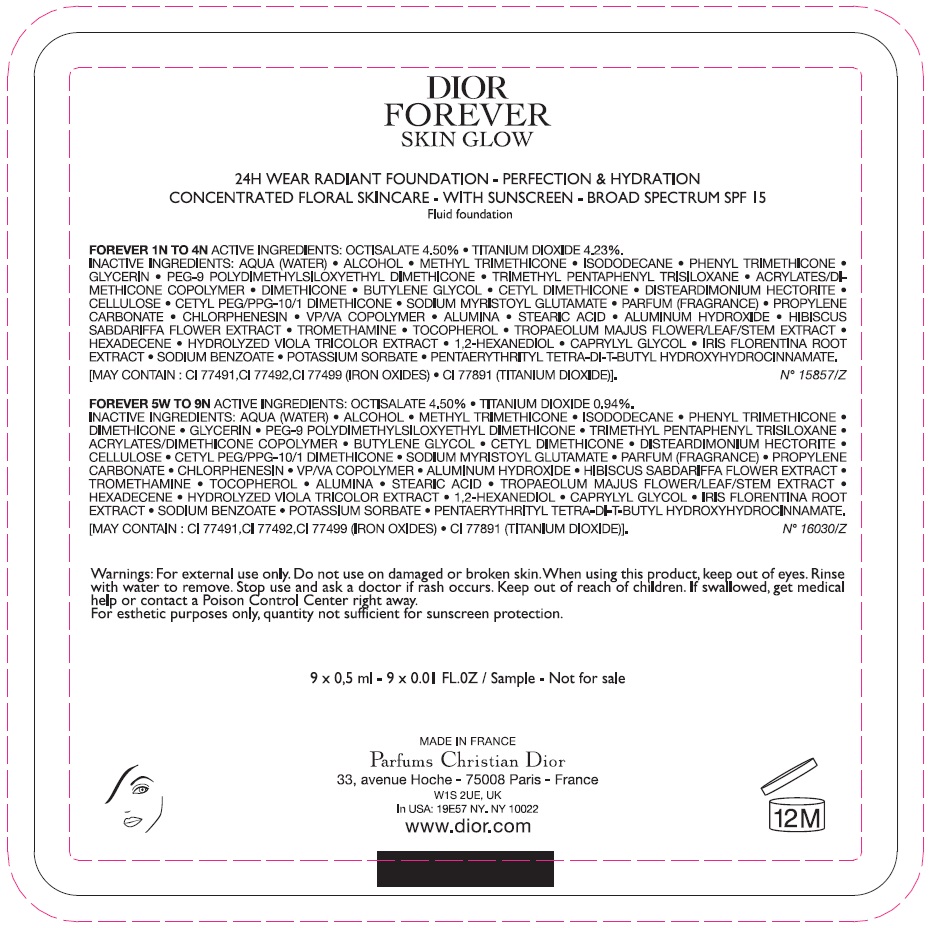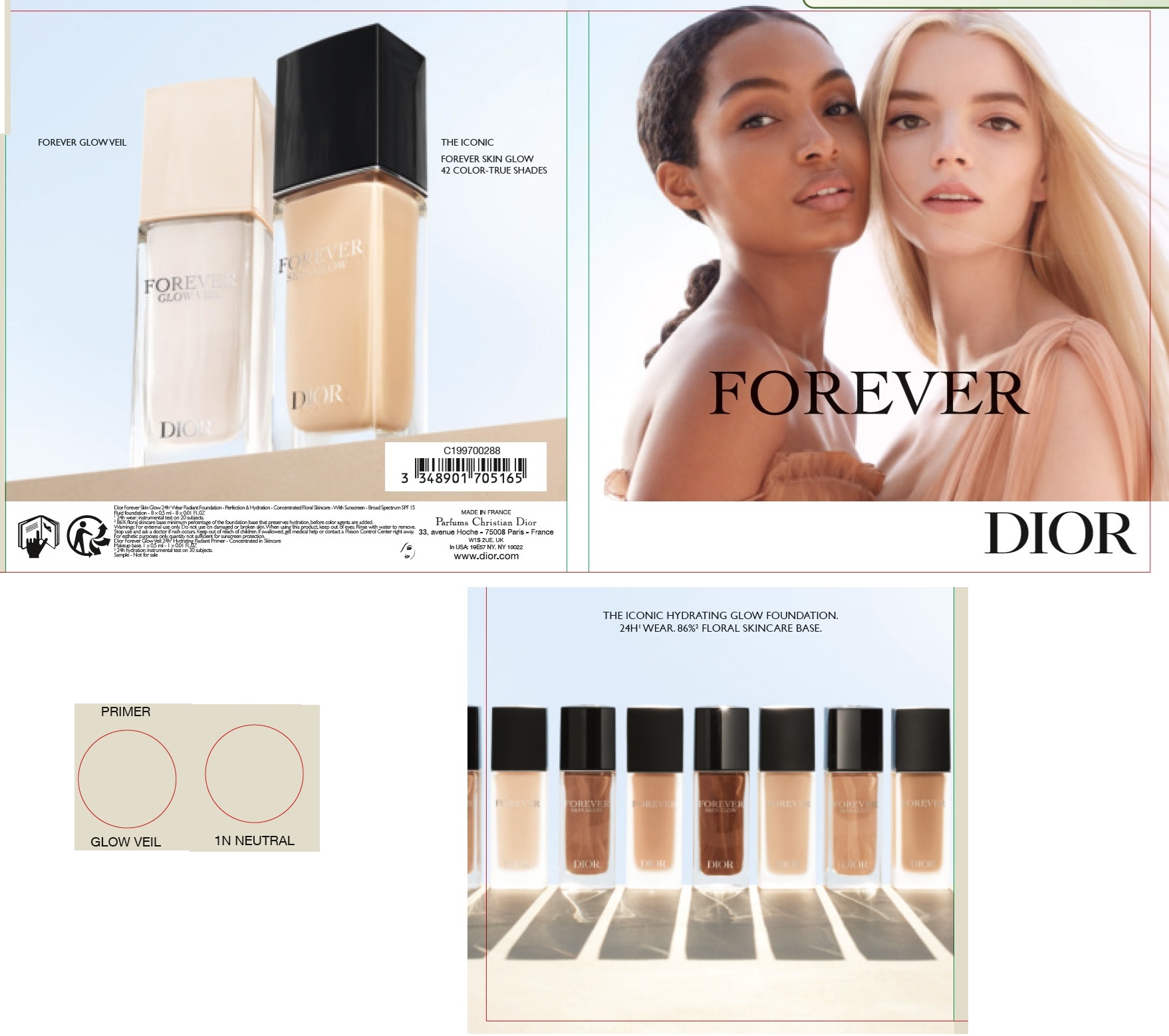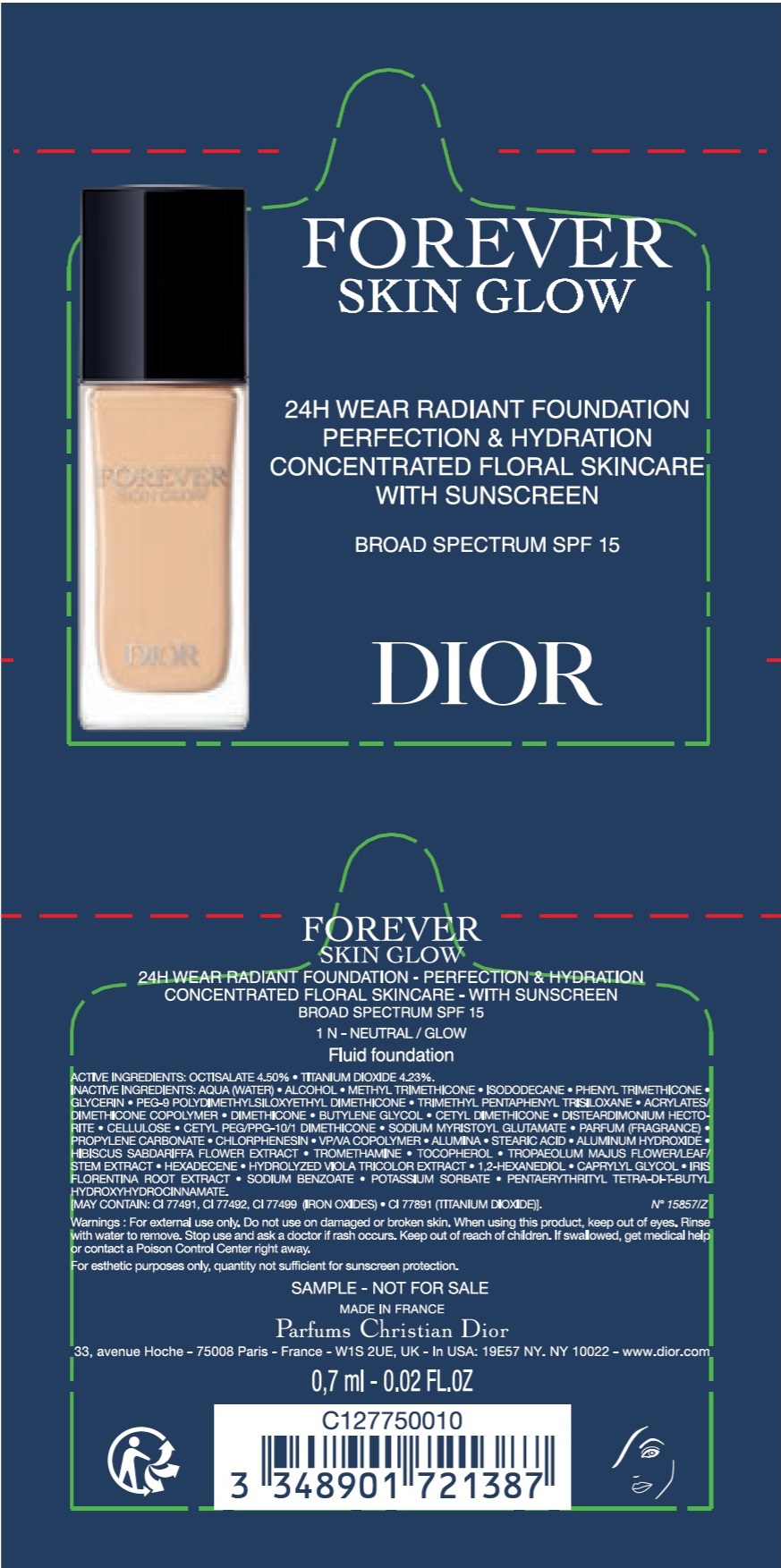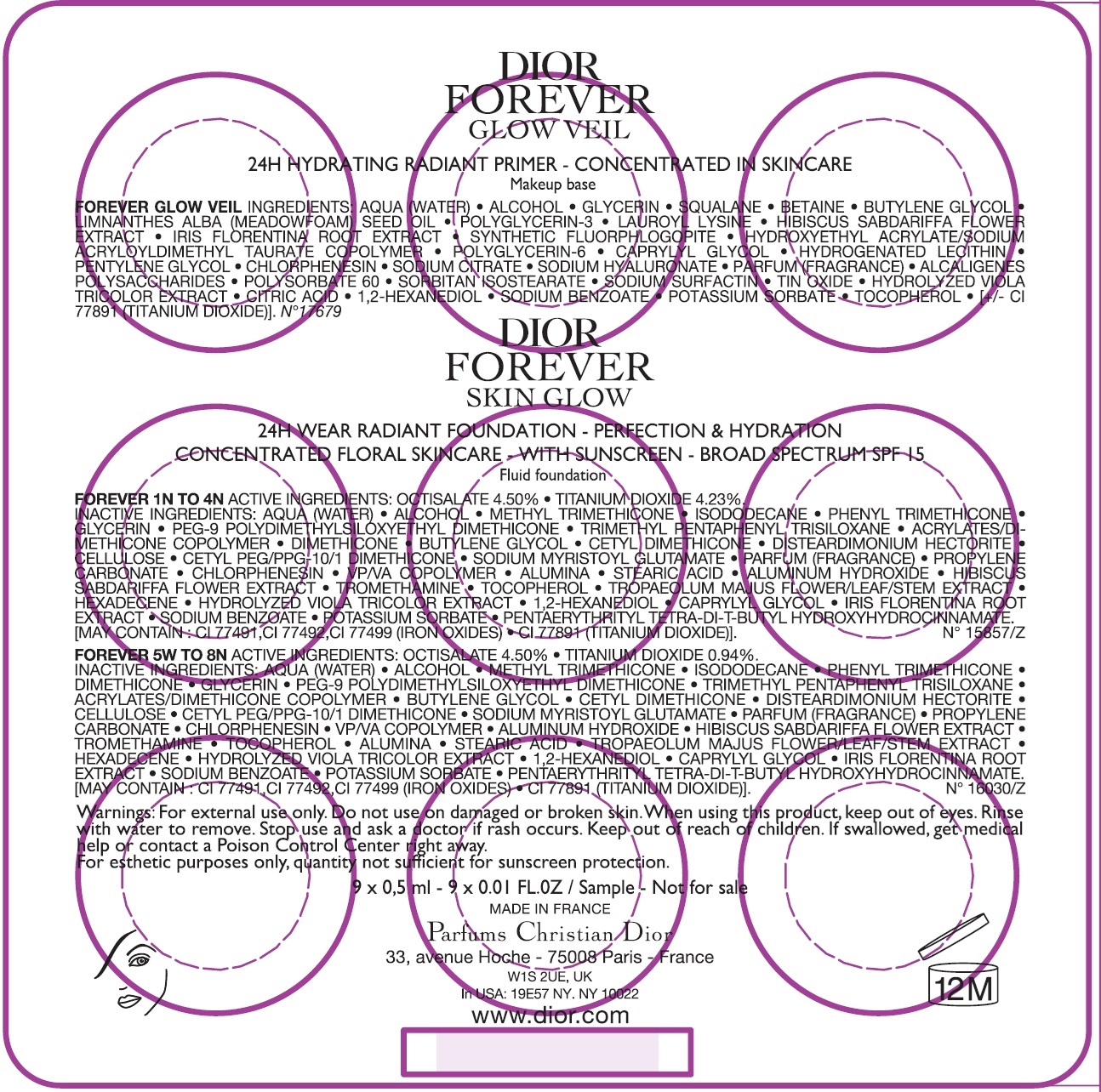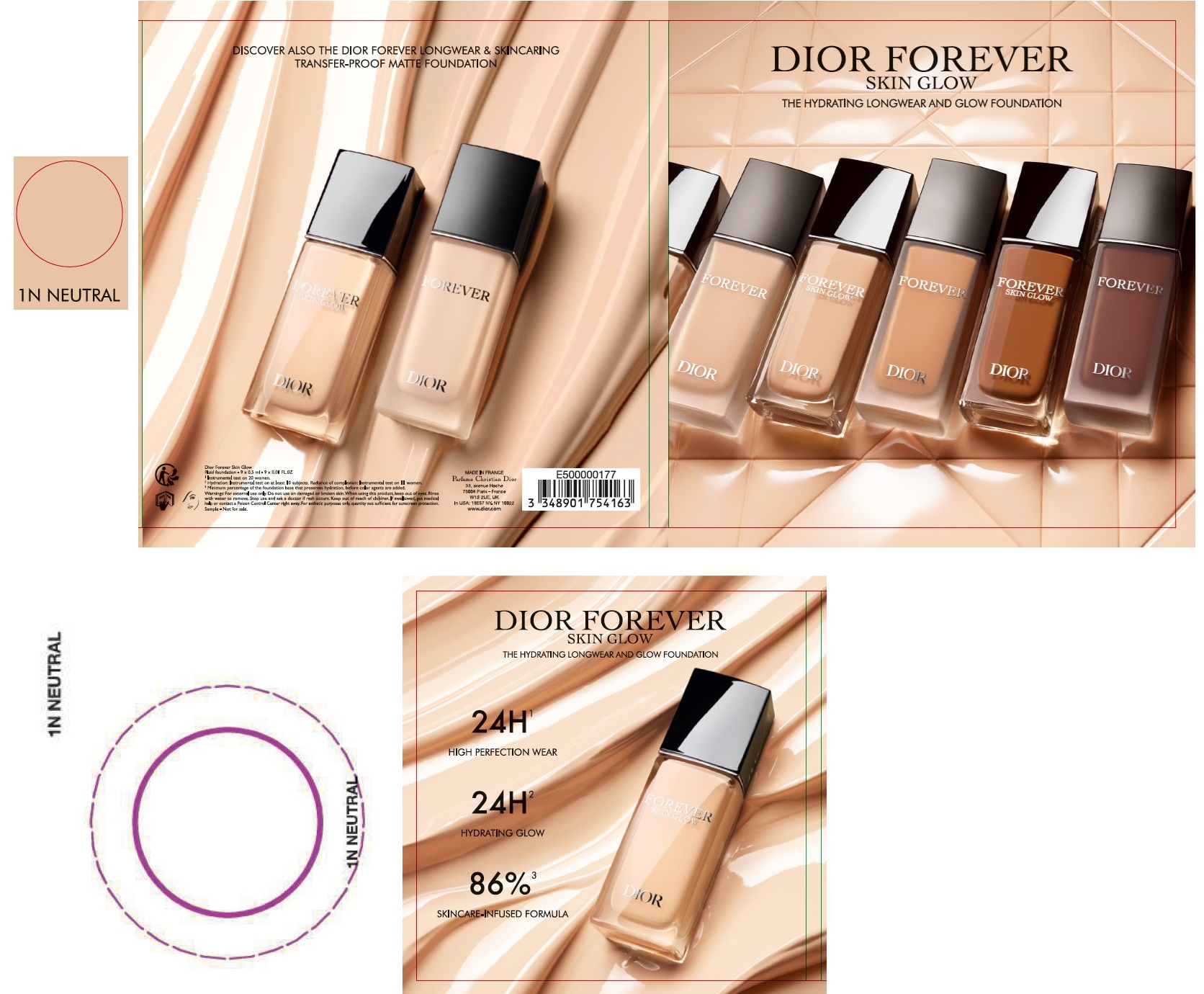 DRUG LABEL: FOREVER SKIN GLOW 24h wear radiant foundation Perfection and hydration Concentrated floral skincare with suncreen Broad spectrum SPF 15 1N
NDC: 61957-3134 | Form: EMULSION
Manufacturer: Parfums Christian Dior
Category: otc | Type: HUMAN OTC DRUG LABEL
Date: 20241125

ACTIVE INGREDIENTS: OCTISALATE 45 mg/1 mL; TITANIUM DIOXIDE 42.3 mg/1 mL
INACTIVE INGREDIENTS: WATER; ALCOHOL; METHYL TRIMETHICONE; ISODODECANE; PHENYL TRIMETHICONE; GLYCERIN; PEG-9 POLYDIMETHYLSILOXYETHYL DIMETHICONE; TRIMETHYL PENTAPHENYL TRISILOXANE; BUTYLENE GLYCOL; DISTEARDIMONIUM HECTORITE; POWDERED CELLULOSE; SODIUM MYRISTOYL GLUTAMATE; PROPYLENE CARBONATE; CHLORPHENESIN; COPOVIDONE K25-31; ALUMINUM OXIDE; STEARIC ACID; ALUMINUM HYDROXIDE; HIBISCUS SABDARIFFA FLOWER; TROMETHAMINE; TOCOPHEROL; TROPAEOLUM MAJUS FLOWERING TOP; HEXADECENE (MIXED ISOMERS); 1,2-HEXANEDIOL; CAPRYLYL GLYCOL; IRIS X GERMANICA NOTHOVAR. FLORENTINA ROOT; SODIUM BENZOATE; POTASSIUM SORBATE; PENTAERYTHRITOL TETRAKIS(3-(3,5-DI-TERT-BUTYL-4-HYDROXYPHENYL)PROPIONATE)

FOREVER SKIN GLOW 24h wear Radiant Foundation Perfection & Hydration Concentrated Floral Skincare with Sunscreen Broad Spectrum SPF 15 1N

Active ingredients

Octinoxate 4.50 %

Titanium Dioxide 4.23 %

Purpose

Sunscreen

Uses

- Helps prevent sunburn.
- If used as directed with other sun protection measures (), decreases the risk of skin cancer and early skin aging caused by the sun. see Directions

Warnings

For external use only.

Do not use

on damaged or broken skin.

When using this product,

keep out of eyes. Rinse with water to remove.

Stop use and ask a doctor if

rash occurs.

Keep out of reach of children.

If swallowed, get medical help or contact a Poison Control Center right away.

Directions

- Apply liberally 15 minutes before sun exposure.
- Reapply at least every 2 hours.
- Use a water-resistant sunscreen if swimming or sweating.
- Spending time in the sun increases your risk of skin cancer and early skin aging. To decrease this risk, regularly use a sunscreen with a broad spectrum SPF of 15 or higher and other sun protection measures including: Sun Protection Measures.
- limit time in the sun, especially from 10 a.m. - 2 p.m.
- wear long-sleeve shirts, pants, hats, and sunglasses.
- Children under 6 months of age: ask a doctor.

Other information

- Protect the product in this container from excessive heat and direct sun.

Inactive ingredients

AQUA (WATER) • ALCOHOL • METHYL TRIMETHICONE • ISODODECANE • PHENYL TRIMETHICONE • GLYCERIN • PEG-9 POLYDIMETHYLSILOXYETHYL DIMETHICONE • TRIMETHTHYL PENTAPHENYL TRISILOXANE • ACRYLATES/DIMETHICONE COPOLYMER DIMETHICONE • BUTYLENE GLYCOL • CETYL DIMETHICONE • DISTEARDIMONIUM HECTORITE • CELLULOSE • CETYL PEG/PPG-10/1 DIMETHICONE • SODIUM MYRISTOYL GLUTAMATE • PARFUM (FRAGRANCE) • PROPYLENE CARBONATE • CHLORPHENESIN • VP/VA COPOLYMER • ALUMINA • STEARIC ACID • ALUMINUM HYDROXIDE • HIBISCUS SABDARIFFA FLOWER EXTRACT • TROMETHAMINE • TOCOPHEROL • TROPAEOLUM MAJUS FLOWER/LEAF/STEM EXTRACT • HEXADECENE • HYDROLYZED VIOLA TRICOLOR EXTRACT • 1,2-HEXANEDIOL • CAPRYLYL GLYCOL • IRIS FLORENTINA ROOT EXTRACT • SODIUM BENZOATE • POTASSIUM SORBATE • PENTAERYTHRITYL TETRA DI-BUTYL HYDROXYHYDROCINNAMATE.

[MAY CONTAIN : CI 77491, CI 77492, CI 77499 (IRON OXIDES), CI 77891 (TITANIUM DIOXIDE)].

N° 15857/Z